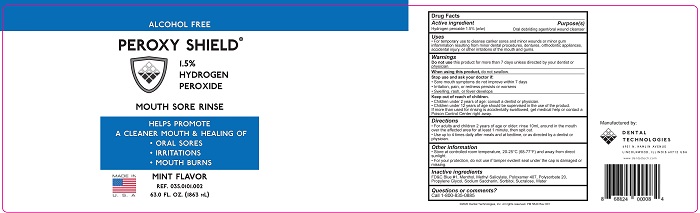 DRUG LABEL: PEROXY SHIELD MOUTH SORE
NDC: 55346-3501 | Form: RINSE
Manufacturer: Dental Technologies, Inc.
Category: otc | Type: HUMAN OTC DRUG LABEL
Date: 20251104

ACTIVE INGREDIENTS: HYDROGEN PEROXIDE 1.5 mL/100 mL
INACTIVE INGREDIENTS: METHYL SALICYLATE; SUCRALOSE; POLOXAMER 407; POLYSORBATE 20; PROPANEDIOL; WATER; SORBITOL SOLUTION 70%; FD&C BLUE NO. 1; SACCHARIN SODIUM; MENTHOL

Peroxy Shield - Mint

Active ingredient

Hydrogen peroxide 1.5% (w/w)

Purpose(s)

Oral debriding agent/oral wound cleaner

Uses

- For temporary use to cleanse canker sores and minor wounds or minor gum inflammation resulting from minor dental procedures, dentures, orthodontic appliances, accidental injury, or other irritations of the mouth and gums.

Warnings

Do not use this product for more than 7 days unless directed by your dentist or physician.

Warnings

When using this product, do not swallow.

Warnings

Stop use and ask your doctor if:

- Sore mouth symptoms do not improve within 7 days
- Irritation, pain, or redness persists or worsens
- Swelling, rash, or fever develops

Warnings

Keep out of reach of children.

- Children under 12 years of age: consult a dentist of physician.
- Children under 12 years of age should be supervised in the use of the product.

If more than used for rinsing is accidentally swallowed, get medical help or contact a Poison Control Center right away.

Directions

- For adults and children under 2 years of age or older: rinse 10mL around in the mouth over the affected area for at least 1 minute, then spit out.
- Use up to 4 times daily after meals and at bedtime, or as directed by a dentist or physician.

Other information

- Store at controlled room temperature, 20-25°C (68-77°F) and away from direct sunlight.
- For your protection, do not use if tamper evident seal under the cap is damaged or missing.

Inactive ingredients

FD&C Blue #1, Menthol, Methyl Salicylate, Poloxamer 407, Polysorbate 20, Propylene Glycol, Sodium Saccharin, Sorbitol, Sucralose, Water

Questions or comments?

Call 1-800-835-0885

Principal Display Panel

ALCOHOL FREE

PEROXY SHIELD®

1.5% HYDROGEN PEROXIDE

MOUTH SORE RINSE

HELPS PROMOTE

A CLEANER MOUTH & HEALING OF

- ORAL SORES
- IRRITATIONS
- MOUTH BURNS

MINT FLAVOR

REF. 035-0101-002

63.0 FL. OZ. (1863 mL)